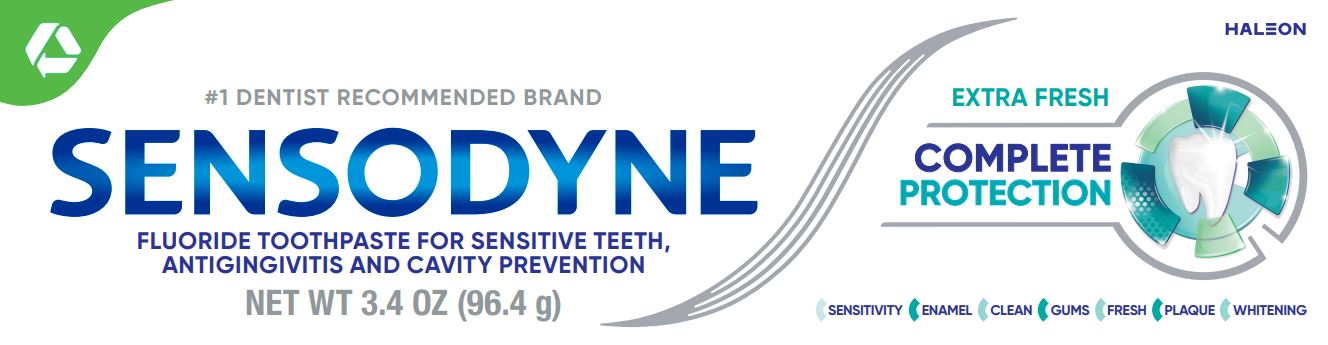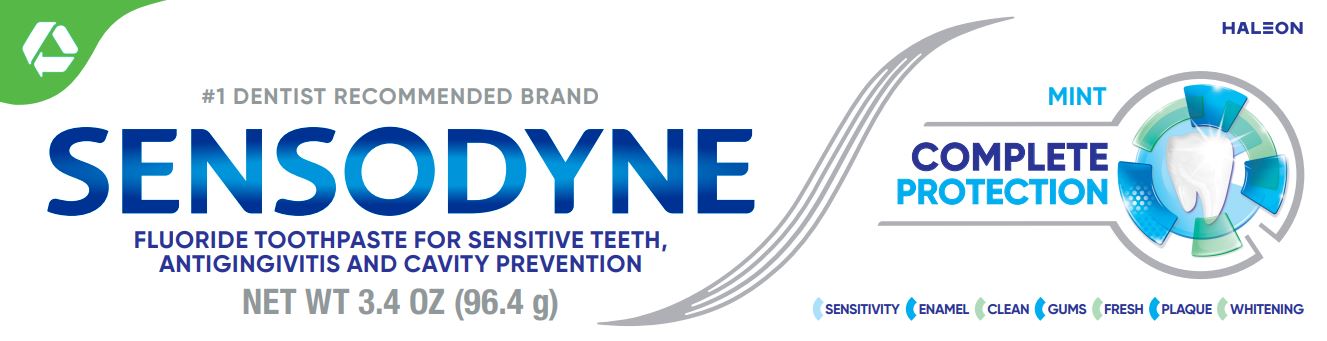 DRUG LABEL: Sensodyne Complete Protection
NDC: 0135-0573 | Form: PASTE
Manufacturer: Haleon US Holdings LLC
Category: otc | Type: HUMAN OTC DRUG LABEL
Date: 20250326

ACTIVE INGREDIENTS: STANNOUS FLUORIDE 1.10 mg/1 g
INACTIVE INGREDIENTS: GLYCERIN; POLYETHYLENE GLYCOL 400; HYDRATED SILICA; SODIUM TRIPOLYPHOSPHATE ANHYDROUS; SODIUM LAURYL SULFATE; TITANIUM DIOXIDE; POLYACRYLIC ACID (250000 MW); SACCHARIN SODIUM; COCAMIDOPROPYL BETAINE

Drug Facts

Active ingredient

Stannous fluoride 0.454% (0.15%w/v fluoride ion)

Purposes

Anticavity, Antigingivitis, Antihypersensitivity

Uses

- aids in the prevention of dental cavities.
- helps prevent gingivitis, an early form of gum disease.
- helps interfere with harmful effects of plaque associated with gingivitis.
- builds increasing protection against painful sensitivity of the teeth to cold, heat, acids, sweets, or contact.

Warnings

Stop use and ask a dentist if:

- the problem persists or worsens. Sensitive teeth may indicate a serious problem that may need prompt care by a dentist.
- pain/sensitivity still persists after 4 weeks of use.
- gingivitis, bleeding, or redness persists for more than 2 weeks.
- you have painful or swollen gums, pus from the gum line, loose teeth, or increasing spacing between the teeth. These may be signs or symptoms of periodontitis, a serious form of gum disease.

Keep out of reach of children.

If more than used for brushing is accidentally swallowed, get medical help or contact a Poison Control Center right away.

Directions

- adults and children 12 years of age and older:
  - apply at least a 1-inch strip of the product onto a soft bristle toothbrush.
  - brush teeth thoroughly for at least 1 minute twice a day (morning and evening), and not more than 3 times a day, or as recommended by a dentist or doctor. Make sure to brush all sensitive areas of the teeth. Minimize swallowing. Spit out after brushing.
- children under 12 years of age: Consult a dentist or doctor.

Other information

- products containing stannous fluoride may produce surface staining of the teeth. Adequate toothbrushing may prevent these stains which are not harmful or permanent and may be removed by your dentist.
- this product is specifically formulated to help prevent staining.
- store below 30°C (86°F)

Inactive ingredients (Mint)

glycerin, PEG-8, hydrated silica, pentasodium triphosphate, flavor, sodium lauryl sulfate, titanium dioxide, polyacrylic acid, sodium saccharin, cocamidopropyl betaine

Inactive ingredients (Extra Fresh)

glycerin, PEG-8, hydrated silica, pentasodium triphosphate, sodium lauryl sulfate, flavor, titanium dioxide, polyacrylic acid, cocamidopropyl betaine, sodium saccharin

Questions or comments?

1-866-844-2797

Additional Information

SENSODYNE COMPLETE PROTECTION

What is tooth sensitivity?

Sensitivity can be a sign that your teeth are vulnerable, as dentin becomes exposed due to enamel loss or gum recession. When exposed dentin comes into contact with hot or cold, sweet or sour, or even your toothbrush, it can trigger the nerve inside the tooth causing a short, sharp pain.

FRESH FEELING

PROTECTS ENAMEL

HELPS WHITEN ENAMEL

PROTECTS AGAINST PLAQUE

BUILDS A PROTECTIVE LAYER OVER SENSITIVE AREAS TO SHIELD YOU FROM PAIN*

CLEAN FEELING

HELPS PREVENT GINGIVITIS

*with twice daily brushing

Why use Sensodyne Complete Protection toothpaste?

This formulation has been specifically developed to deliver all the toothpaste benefits your sensitive teeth need. Brush twice a day with Sensodyne Complete Protection toothpaste.

ALWAYS FOLLOW THE LABEL

Trademarks are owned by or licensed to the Haleon group of companies.

©2023 Haleon group of companies or its licensor.

Distributed by: Haleon, Warren, NJ 07059

Pat. Info www.productpats.com

† Recycling facilities for this product may not exist in your area

CARTON RECYCLE

TUBE RECYCLE

CAP CHECK LOCALLY

Principal Display Panel (Mint)

#1 DENTIST RECOMMENDED BRAND

SENSODYNE

FLUORIDE TOOTHPASTE FOR SENSITIVE TEETH,
ANTIGINGIVITIS AND CAVITY PREVENTION

NET WT 3.4 OZ (96.4 g)

MINT

COMPLETE PROTECTION

SENSITIVITY

ENAMEL

CLEAN

GUMS

FRESH

PLAQUE

WHITENING

62000000207019

Principal Display Panel (Extra Fresh)

#1 DENTIST RECOMMENDED BRAND

SENSODYNE

TOOTHPASTE FOR SENSITIVE TEETH,
ANTIGINGIVITIS AND CAVITY PREVENTION

NET WT 3.4 OZ (96.4 g)

EXTRA FRESH

COMPLETE PROTECTION

SENSITIVITY

ENAMEL

CLEAN

GUMS

FRESH

PLAQUE

ENAMEL

WHITENING

62000000207024